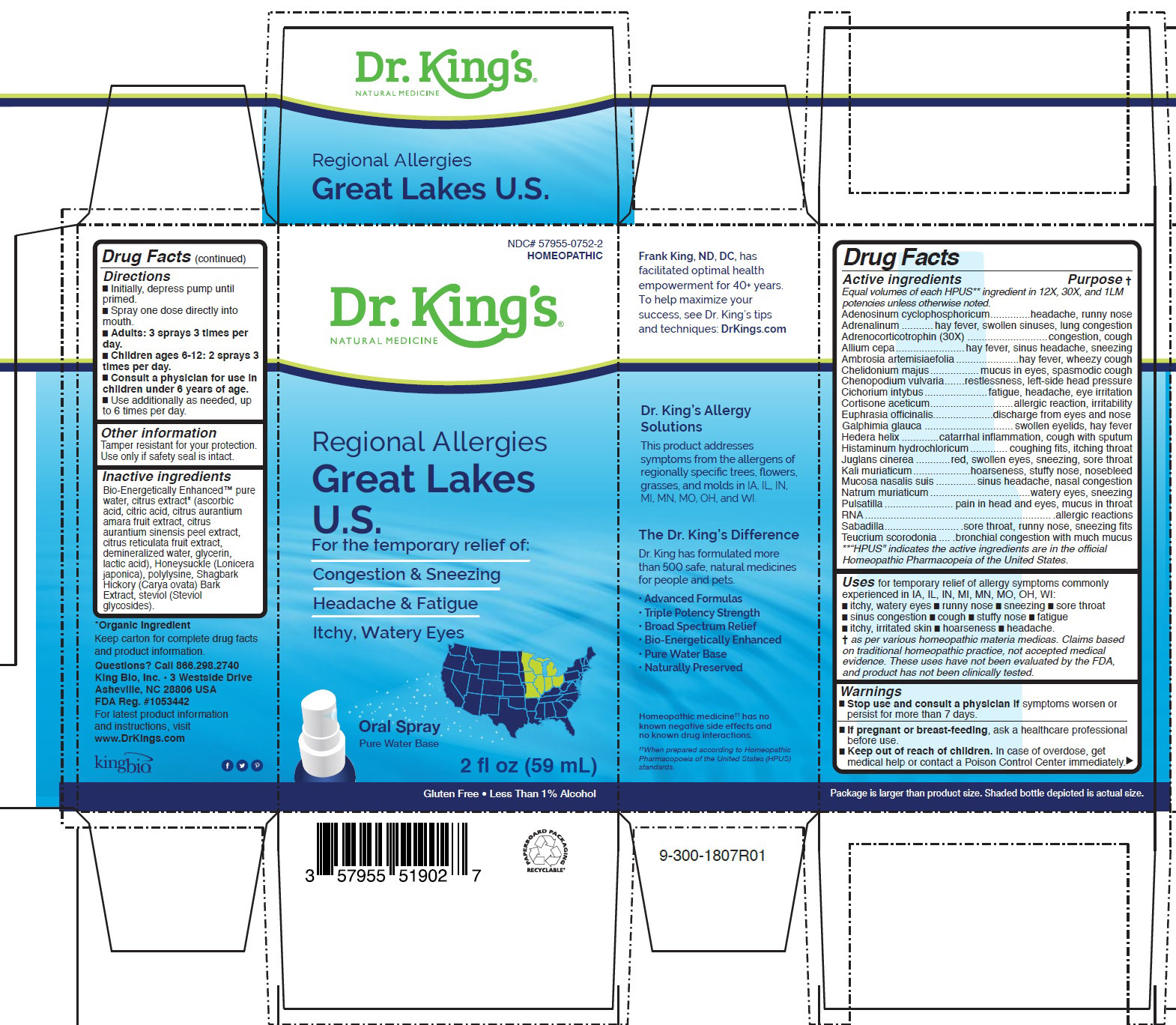 DRUG LABEL: Regional Allergies Great Lakes U.S.
NDC: 57955-0752 | Form: LIQUID
Manufacturer: King Bio Inc.
Category: homeopathic | Type: HUMAN OTC DRUG LABEL
Date: 20200708

ACTIVE INGREDIENTS: ADENOSINE CYCLIC PHOSPHATE 12 [hp_X]/59 mL; EPINEPHRINE 12 [hp_X]/59 mL; CORTICOTROPIN 30 [hp_X]/59 mL; ONION 12 [hp_X]/59 mL; AMBROSIA ARTEMISIIFOLIA 12 [hp_X]/59 mL; CHELIDONIUM MAJUS 12 [hp_X]/59 mL; CHENOPODIUM VULVARIA 12 [hp_X]/59 mL; CHICORY ROOT 12 [hp_X]/59 mL; CORTISONE ACETATE 12 [hp_X]/59 mL; EUPHRASIA STRICTA 12 [hp_X]/59 mL; GALPHIMIA GLAUCA FLOWERING TOP 12 [hp_X]/59 mL; HEDERA HELIX FLOWERING TWIG 12 [hp_X]/59 mL; HISTAMINE DIHYDROCHLORIDE 12 [hp_X]/59 mL; JUGLANS CINEREA BRANCH BARK/ROOT BARK 12 [hp_X]/59 mL; POTASSIUM CHLORIDE 12 [hp_X]/59 mL; SUS SCROFA NASAL MUCOSA 12 [hp_X]/59 mL; SODIUM CHLORIDE 12 [hp_X]/59 mL; PULSATILLA PATENS WHOLE 12 [hp_X]/59 mL; SACCHAROMYCES CEREVISIAE RNA 12 [hp_X]/59 mL; SCHOENOCAULON OFFICINALE SEED 12 [hp_X]/59 mL; TEUCRIUM SCORODONIA FLOWERING TOP 12 [hp_X]/59 mL
INACTIVE INGREDIENTS: WATER; CARYA OVATA BARK; CITRUS BIOFLAVONOIDS; LONICERA JAPONICA FLOWER; POLYEPSILON-LYSINE (4000 MW); REBAUDIOSIDE A

Regional Allergies Great Lakes U.S.

ACTIVE INGREDIENT

Drug Facts__________________________________________________________________________________________________________

HPUS active ingredients: Adenosinum cyclophosphoricum, Adrenalinum, Adrenocorticotrophin(30X), Allium cepa, Ambrosia artemisiaefolia, Chelidonium majus, Chenopodium vulvaria, Cichorium intybus, Cortisone aceticum, Euphrasia officinalis, Galphimia glauca, Hedera helix, Histaminum hydrochloricum, Juglans cinerea, Kali muriaticum, Mucosa nasalis suis, Natrum muriaticum, Pulsatilla, RNA, Sabadilla, Teucrium scorodonia.

INDICATIONS AND USAGE

Uses for temporary relief of allergy symptoms commonly experienced in IA, IL, IN, MI, MN, MO, OH, WI: •itchy, watery eyes •runny nose •sneezing •sore throat •sinus congestion •cough •stuffy nose •fatigue •itchy, irritated skin •hoarseness •headache.

† as per various homeopathic materia medicas. These uses have not been evaluated by the FDA, and product has not been clinically tested.

Warnings

Stop use and consult a physician if symptoms worsen or
persist for more than 7 days.

PREGNANCY OR BREAST FEEDING

If pregnant or breast-feeding, ask a healthcare professional before use.

Keep out of reach of children. In case of overdose, get medical help or contact a Poison Control Center immediately.

Directions
█ Initially, depress pump until primed.
█ Spray one dose directly into mouth.
█ Adults: 3 sprays 3 times per day.
█ Children ages 6-12: 2 sprays 3 times per day.
█ Consult a physician for use in children under 6 years of age.
█ Use additionally as needed, up to 6 times per day.

Other information: Tamper resistant for your protection. Use only if safety seal is intact.

Inactive Ingredients:

Bio-Energetically Enhanced™ pure
water, citrus extract* (ascorbic
acid, citric acid, citrus aurantium
amara fruit extract, citrus
aurantium sinensis peel extract,
citrus reticulata fruit extract,
demineralized water, glycerin,
lactic acid), Honeysuckle (Lonicera
japonica), polylysine, Shagbark
Hickory (Carya ovata) Bark
Extract, steviol (Steviol
glycosides).

Drug Facts

____________________________________________________________________________________________________________

HPUS* active ingredients Purpose

Equal volumes of each HPUS** ingredient in 12X, 30X, and 1LM
potencies unless otherwise noted.
Adenosinum cyclophosphoricum..............headache, runny nose
Adrenalinum ...........hay fever, swollen sinuses, lung congestion
Adrenocorticotrophin (30X) ............................congestion, cough
Allium cepa........................hay fever, sinus headache, sneezing
Ambrosia artemisiaefolia......................hay fever, wheezy cough
Chelidonium majus.................mucus in eyes, spasmodic cough
Chenopodium vulvaria.......restlessness, left-side head pressure
Cichorium intybus......................fatigue, headache, eye irritation
Cortisone aceticum.............................allergic reaction, irritability
Euphrasia officinalis.....................discharge from eyes and nose
Galphimia glauca ...............................swollen eyelids, hay fever
Hedera helix .............catarrhal inflammation, cough with sputum
Histaminum hydrochloricum............. coughing fits, itching throat
Juglans cinerea ............red, swollen eyes, sneezing, sore throat
Kali muriaticum....................hoarseness, stuffy nose, nosebleed
Mucosa nasalis suis ..............sinus headache, nasal congestion
Natrum muriaticum...................................watery eyes, sneezing
Pulsatilla........................ pain in head and eyes, mucus in throat
RNA..................................................................allergic reactions
Sabadilla...........................sore throat, runny nose, sneezing fits
Teucrium scorodonia .... .bronchial congestion with much mucus
**“HPUS” indicates the active ingredients are in the official
Homeopathic Pharmacopeia of the United States.

Questions? Call 866.298.2740
King Bio, Inc. • 3 Westside Drive
Asheville, NC 28806 USA
FDA Reg. #1053442

For latest product information
and instructions, visit
www.DrKings.com